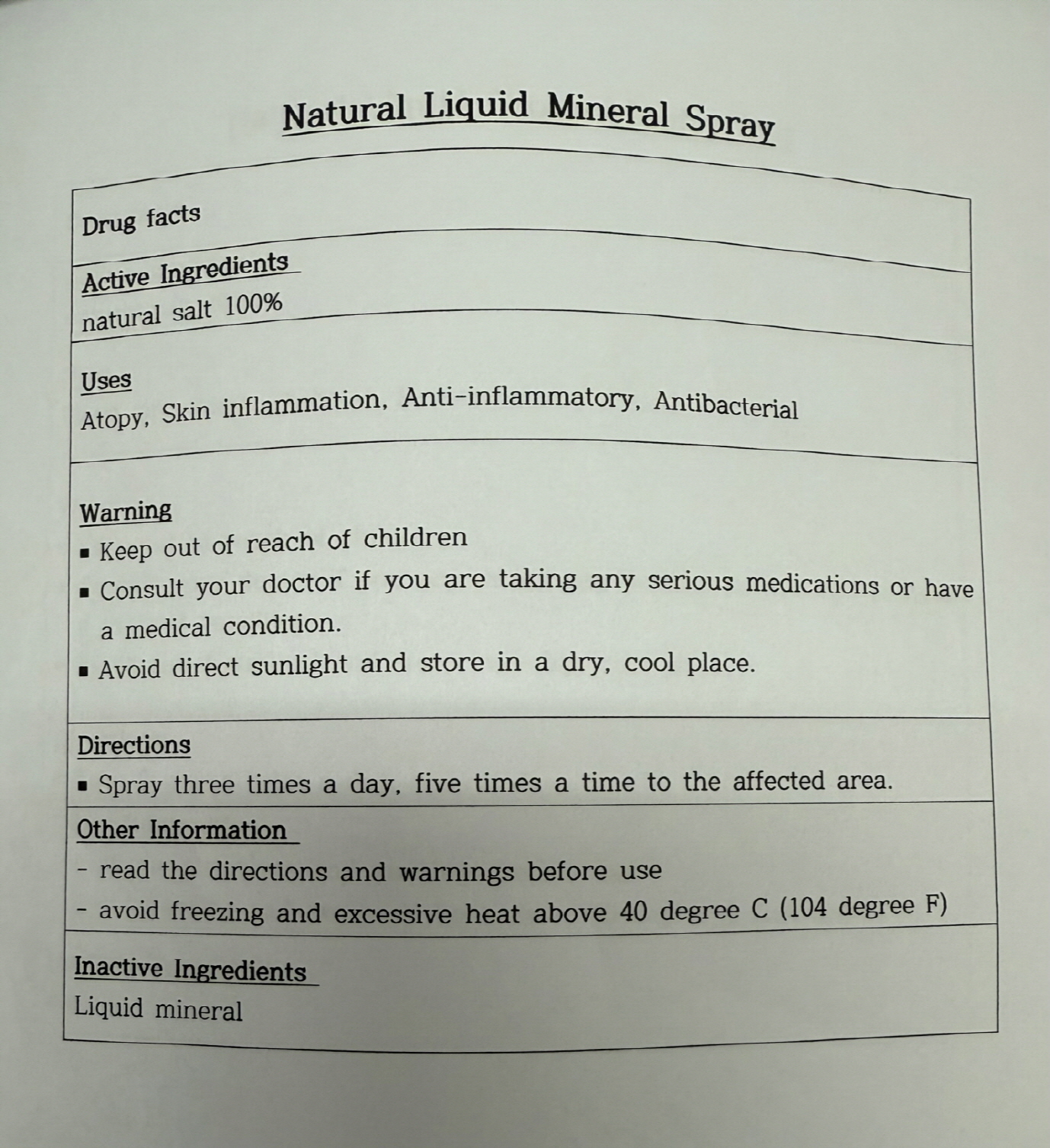 DRUG LABEL: NATURAL LIQUIDMINERALSPRAY
NDC: 87034-0002 | Form: LIQUID
Manufacturer: K-LA-KO Co.,LTD
Category: otc | Type: HUMAN OTC DRUG LABEL
Date: 20250824

ACTIVE INGREDIENTS: SODIUM CHLORIDE 100 g/100 mL
INACTIVE INGREDIENTS: WATER

Drug Facts

ACTIVE INGREDIENT

NATURAL SALT 100%

INACTIVE INGREDIENT

Liquid mineral

PURPOSE

Atopy, Skin inflammation, Anti-inflammatory, Antibacterial

keep out of reach of the children

INDICATIONS AND USAGE

Spray three times a day, five times a time to the affected area.

WARNINGS

Consult your doctor if you are taking any serious medication or have a medical condition

Avoid direct sunlight and store in a dry, cool place.

Read the directions and warnings before use.

Avoid freezing and excessive heat abouve 40 degree C (104 degree F)

DOSAGE AND ADMINISTRATION

topical use only